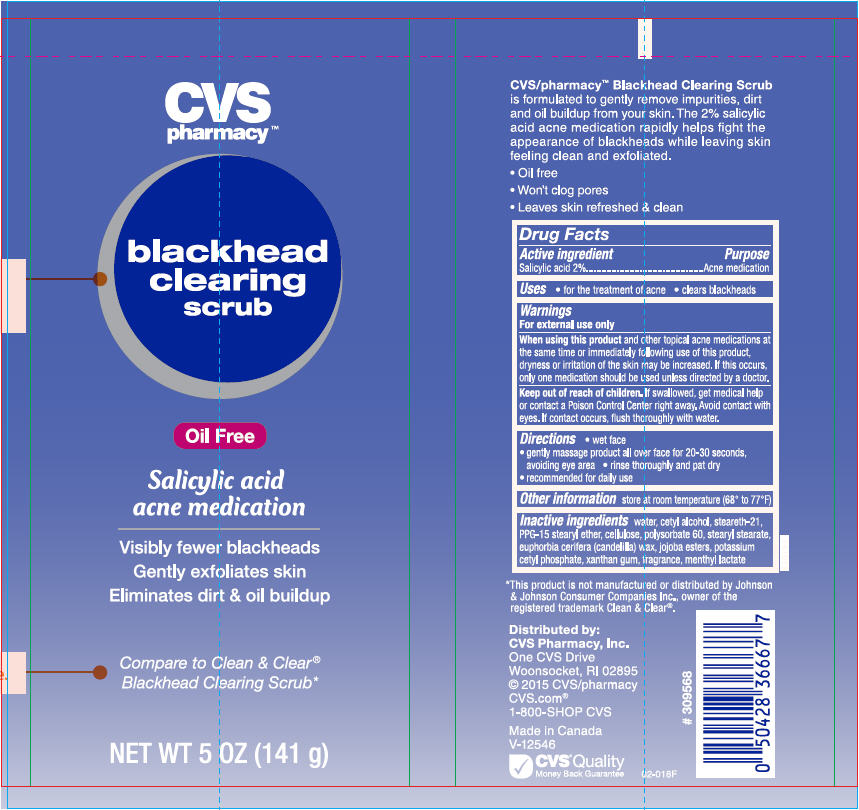 DRUG LABEL: CVS Health Blackhead Clearing Scrub 
NDC: 69842-480 | Form: CREAM
Manufacturer: CVS Health
Category: otc | Type: HUMAN OTC DRUG LABEL
Date: 20220124

ACTIVE INGREDIENTS: Salicylic Acid 20 mg/1 g
INACTIVE INGREDIENTS: Water; Cetyl Alcohol; Steareth-21; PPG-15 Stearyl Ether; Powdered Cellulose; Polysorbate 60; Stearyl Stearate; Candelilla Wax; Hydrolyzed Jojoba Esters (Acid Form); Potassium Cetyl Phosphate; Xanthan Gum; Methyl Lactate, (-)-

CVS Health Blackhead Clearing Scrub
Acne Medication

Drug Facts

Active ingredients

Salicylic Acid 2.0%

Purpose

Acne Medication

Uses

For the treatment of Acne

♦ clears blackheads

Warnings

For external use only

Ask a doctor or pharmacist before use if you are using other topical acne medications at the same time or immediately following use of this product. This may increase dryness or irritation of the skin. If this occurs, only one medication should be used unless directed by a doctor.

When using this product

♦ skin irritation and dryness is more likely to occur if you use another topical acne medication at the same time. If irritation occurs, only use one topical acne medication at a time
♦ avoid contact with eyes. If contact occurs, flush thoroughly with water.

Keep out of reach of children. If swallowed, get medical help or contact a Poison Control Center right away.

Directions

♦ wet face
♦ gently massage product all over face for 20-30 seconds, avoid eye area
♦ rinse thoroughly and pat dry recommended for daily use.

Other information

Store at room temperature (68°F – 77°F).

Inactive ingredients

Water, Cetyl Alcohol, Steareth-21, PPG-15 Stearyl Ether, Cellulose, Polysorbate 60, Stearyl Stearate, Euphorbia Cerifera (Candelilla) Wax, Jojoba Esters, Potassium Cetyl Phosphate, Xanthan Gum, Fragrance, Methyl Lactate.

Distributed by:
CVS Pharmacy, Inc.
One CVS Drive
Woonsocket, RI 02895

PRINCIPAL DISPLAY PANEL - 141 g Tube Label

CVS
pharmacy™

blackhead
clearing
scrub

Oil Free

Salicylic acid
acne medication

Visibly fewer blackheads
Gently exfoliates skin
Eliminates dirt & oil buildup

Compare to Clean & Clear®
Blackhead Clearing Scrub*

NET WT 5 OZ (141 g)